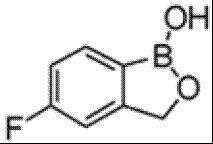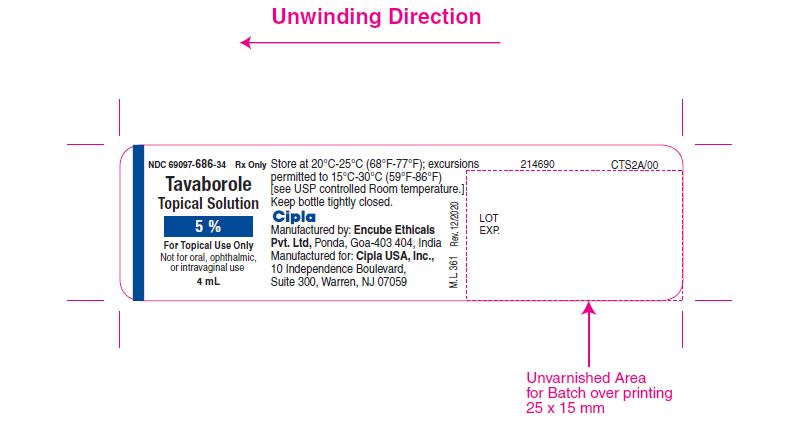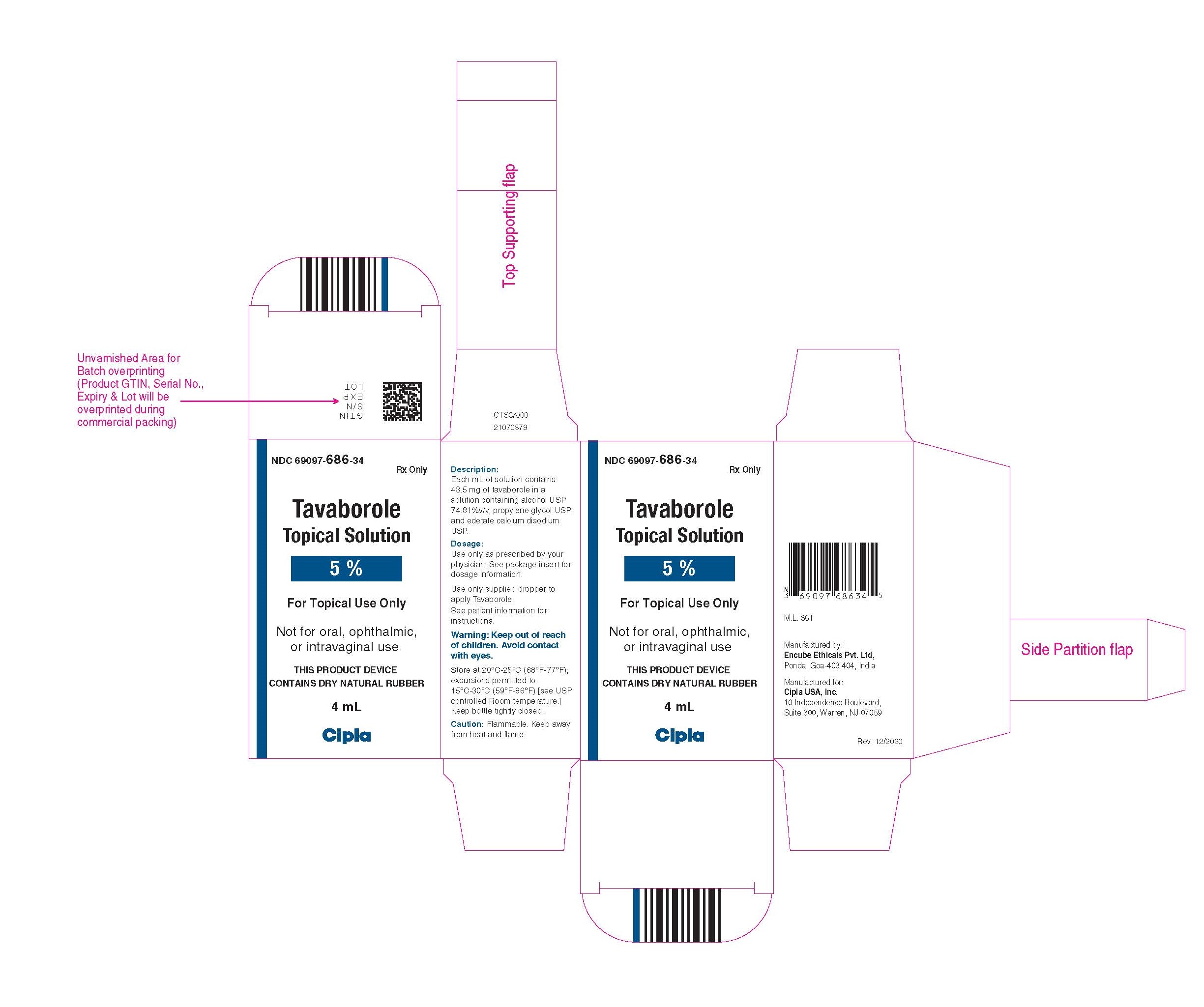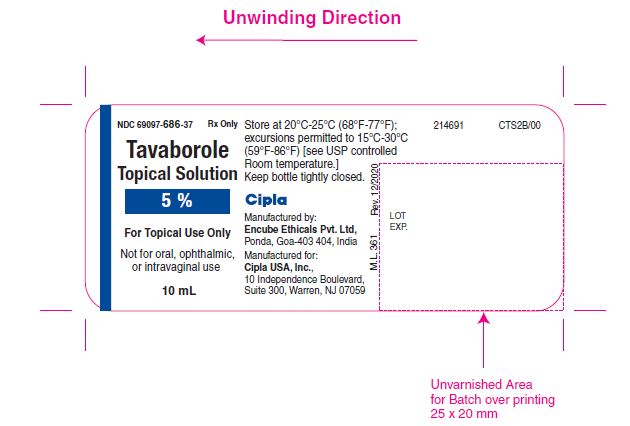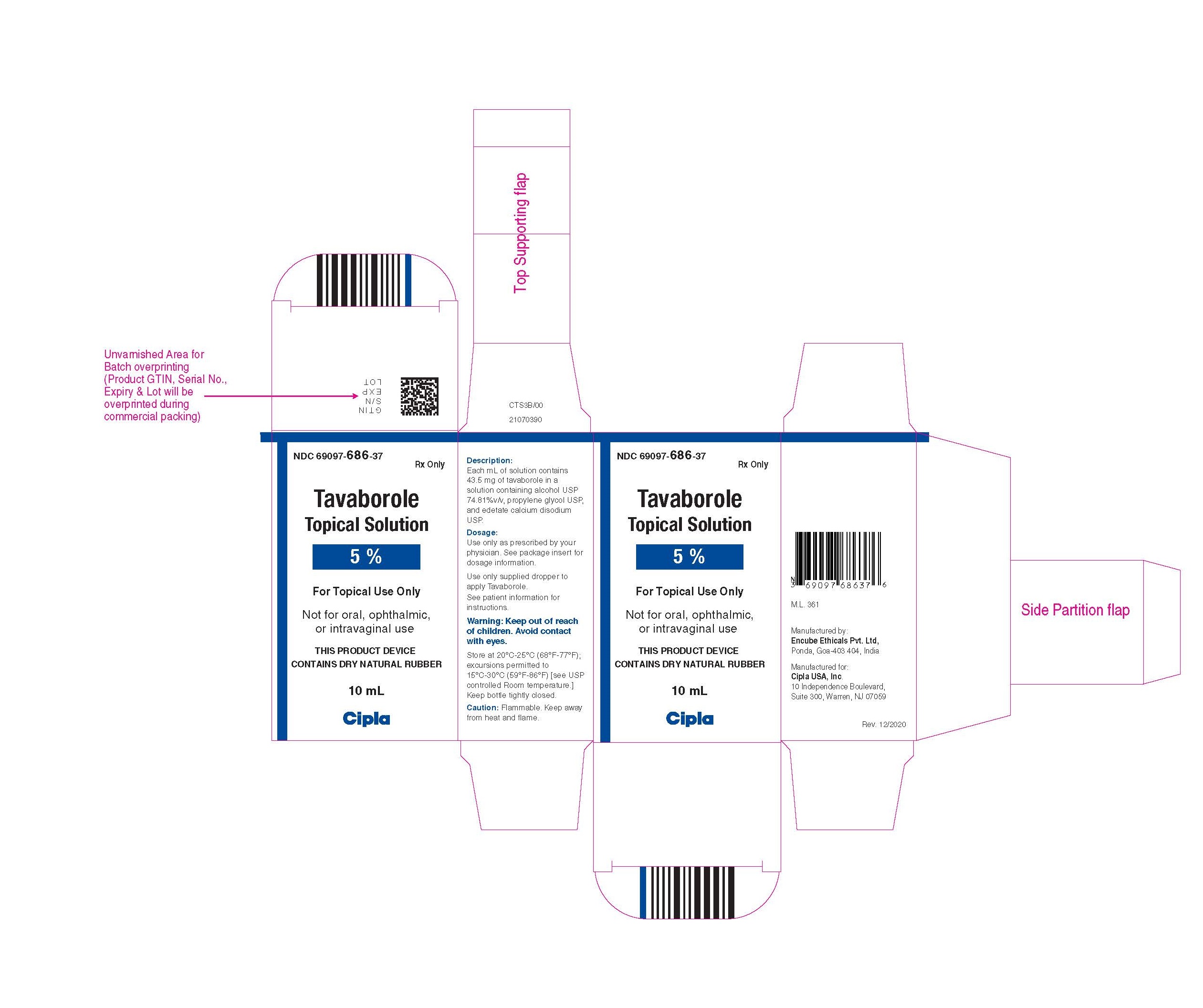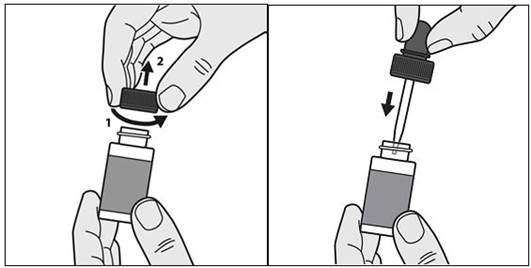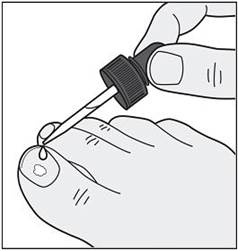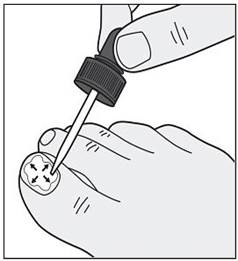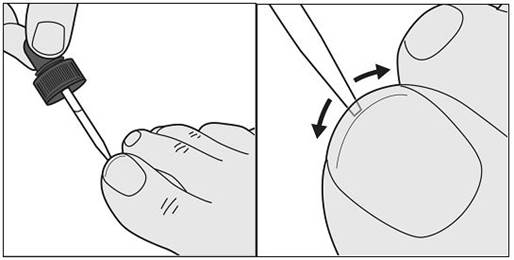 DRUG LABEL: TAVABOROLE
NDC: 69097-686 | Form: SOLUTION
Manufacturer: Cipla USA Inc.
Category: prescription | Type: HUMAN PRESCRIPTION DRUG LABEL
Date: 20251219

ACTIVE INGREDIENTS: TAVABOROLE 43.5 mg/1 mL
INACTIVE INGREDIENTS: ALCOHOL; EDETATE CALCIUM DISODIUM; PROPYLENE GLYCOL

HIGHLIGHTS OF PRESCRIBING INFORMATION

These highlights do not include all the information needed to use TAVABOROLE TOPICAL SOLUTION safely and effectively. See full prescribing information for TAVABOROLE TOPICAL SOLUTION.
TAVABOROLE topical solution
Initial U.S. Approval: 2014

1 INDICATIONS AND USAGE

Tavaborole topical solution is an oxaborole antifungal indicated for the topical treatment of onychomycosis of the toenails due to Trichophyton rubrum or Trichophyton mentagrophytes. (1)

2 DOSAGE AND ADMINISTRATION

- Apply tavaborole topical solution to affected toenails once daily for 48 weeks. (2)
- Tavaborole topical solution should be applied to the entire toenail surface and under the tip of each toenail being treated. (2)
- For topical use only. (2)
- Not for oral, ophthalmic, or intravaginal use. (2)

3 DOSAGE FORMS AND STRENGTHS

Solution, 5%. (3)

4 CONTRAINDICATIONS

None. (4)

6 ADVERSE REACTIONS

Common adverse reactions occurring in ≥1% in subjects treated with tavaborole topical solution included application site exfoliation, ingrown toenail, application site erythema, and application site dermatitis. (6.1)

To report SUSPECTED ADVERSE REACTIONS, contact Cipla Ltd at 1-866-604-3268 or FDA at 1-800-FDA-1088 or www.fda.gov/medwatch.

FULL PRESCRIBING INFORMATION

1 INDICATIONS AND USAGE

Tavaborole topical solution, 5% is an oxaborole antifungal indicated for the treatment of onychomycosis of the toenails due to Trichophyton rubrum or Trichophyton mentagrophytes.

2 DOSAGE AND ADMINISTRATION

Apply tavaborole topical solution to affected toenails once daily for 48 weeks.

Tavaborole topical solution should be applied to the entire toenail surface and under the tip of each toenail being treated.

Tavaborole topical solution is for topical use only and not for oral, ophthalmic, or intravaginal use.

3 DOSAGE FORMS AND STRENGTHS

Tavaborole topical solution, 5% is a clear, colorless alcohol-based solution. Each milliliter of solution contains 43.5 mg (5% w/w) of tavaborole.

4 CONTRAINDICATIONS

None.

6 ADVERSE REACTIONS

6.1 Clinical Trials Experience

Because clinical trials are conducted under widely varying conditions, adverse reaction rates observed in the clinical trials of a drug cannot be directly compared to rates in the clinical trials of another drug and may not reflect the rates observed in practice.

In two clinical trials, 791 subjects were treated with tavaborole topical solution. The most commonly reported adverse reactions are listed below (Table 1).

Table 1: Adverse Reactions Occurring in ≥1% of Tavaborole Topical Solution, 5%-Treated Subjects and at a Greater Frequency than Observed with Vehicle
Preferred Term | Tavaborole Topical Solution N=791 n (%) | Vehicle N=395 n (%)
Application site exfoliation | 21 (2.7%) | 1 (0.3%)
Ingrown toenail | 20 (2.5%) | 1 (0.3%)
Application site erythema | 13 (1.6%) | 0 (0%)
Application site dermatitis | 10 (1.3%) | 0 (0%)

6.2 Postmarketing Experience

The following adverse reactions have been identified during postmarketing use of tavaborole topical solution. Because these reactions are reported voluntarily from a population of uncertain size, it is not always possible to reliably estimate their frequency or establish a causal relationship to drug product exposure:

Hypersensitivity; contact allergy

8 USE IN SPECIFIC POPULATIONS

8.1 Pregnancy

Risk Summary

There are no available data on tavaborole topical solution use in pregnant women to inform a drug associated risk for major birth defects, miscarriage or adverse maternal or fetal outcomes. In oral animal reproductive studies, administration of tavaborole during the period of organogenesis resulted in embryofetal toxicity and malformations at 570 times the Maximum Recommended Human Dose (MRHD) based on Area Under the Curve (AUC) comparisons in rats and embryofetal toxicity at 155 times the MRHD based on AUC comparisons in rabbits. Embryofetal toxicity was noted following dermal administration in rabbits up to 36 times the MRHD based on AUC comparisons [see Data].

The background risk of major birth defects and miscarriage for the indicated population is unknown. All pregnancies carry some risk of birth defect, loss, or other adverse outcomes. The background risk of major birth defects in the U.S. general population is 2% to 4% and of miscarriage is 15% to 20% of clinically recognized pregnancies.

Data

Animal Data

Oral administration:

In an oral embryofetal development study in rats, oral doses of 30, 100, and 300 mg/kg/day tavaborole were administered during the period of organogenesis (gestational days 6-19) to pregnant female rats. In the presence of maternal toxicity, embryofetal toxicity (increased embryofetal resorption and/or deaths) and drug-related skeletal malformations and variations suggestive of delayed development (i.e., a delay in ossification) were noted in fetuses at 300 mg/kg/day tavaborole [570 times the MRHD based on AUC comparisons]. No developmental toxicity was noted in rats at 100 mg/kg/day tavaborole (26 times the MRHD based on AUC comparisons).

In an oral embryofetal development study in rabbits, oral doses of 15, 50, and 150 mg/kg/day tavaborole were administered during the period of organogenesis (gestational days 7-19) to pregnant female rabbits. In the presence of maternal toxicity, excessive embryofetal mortality due to post-implantation loss was noted at 150 mg/kg/day tavaborole. No drug related malformations were noted in rabbits at 150 mg/kg/day tavaborole (155 times the MRHD based on AUC comparisons). No embryofetal mortality was noted in rabbits at 50 mg/kg/day tavaborole (16 times the MRHD based on AUC comparisons).

In an oral pre- and post-natal development study in rats, oral doses of 15, 60, and 100 mg/kg/day tavaborole were administered from the beginning of organogenesis (gestation day 6) through the end of lactation (lactation day 20). In the presence of minimal maternal toxicity, no embryofetal toxicity or effects on postnatal development were noted at 100 mg/kg/day (29 times the MRHD based on AUC comparisons).

Topical administration:

In a dermal embryofetal development study in rabbits, topical doses of 1%, 5%, and 10% tavaborole solution were administered during the period of organogenesis (gestational days 6-28) to pregnant female rabbits. A dose dependent increase in dermal irritation at the treatment site was noted at 5% and 10% tavaborole solution. A decrease in fetal bodyweight was noted at 10% tavaborole solution. No drug related malformations were noted in rabbits at 10% tavaborole solution (36 times the MRHD based on AUC comparisons). No embryofetal toxicity was noted in rabbits at 5% tavaborole solution (26 times the MRHD based on AUC comparisons).

8.2 Lactation

Risk Summary

There is no information available on the presence of tavaborole in human milk, the effects of the drug on the breastfed infant or the effects of the drug on milk production after topical application of tavaborole to women who are breastfeeding. Tavaborole is systemically absorbed. The lack of clinical data during lactation precludes a clear determination of the risk of tavaborole topical solution to a breastfed infant. Therefore, the developmental and health benefits of breastfeeding should be considered along with the mother's clinical need for tavaborole topical solution and any potential adverse effects on the breastfed child from tavaborole topical solution or from the underlying maternal condition.

8.4 Pediatric Use

The safety and efficacy of tavaborole topical solution were established in patients 6 years of age and older. Use of tavaborole topical solution in these age groups is supported by evidence from adequate and well-controlled studies of tavaborole topical solution in adults with additional data from an open-label pharmacokinetics study of tavaborole in subjects 12 years to less than 17 years old [see Clinical Pharmacology (12.3)].

8.5 Geriatric Use

In clinical trials of 791 subjects who were exposed to tavaborole topical solution, 19% were 65 years of age and over, while 4% were 75 years of age and over. No overall differences in safety or effectiveness were observed between these subjects and younger subjects, but greater sensitivity of some older individuals cannot be ruled out.

11 DESCRIPTION

Tavaborole topical solution, 5% contains tavaborole, 5% (w/w) in a clear, colorless alcohol-based solution for topical use. The active ingredient, tavaborole, is an oxaborole antifungal with the chemical name of 5-fluoro-1,3-dihydro-1-hydroxy-2,1-benzoxaborole. The chemical formula is C7H6BFO2, the molecular weight is 151.93 and the structural formula is:

Tavaborole is a white to off-white powder. It is slightly soluble in water and freely soluble in ethanol and propylene glycol.

Each mL of tavaborole topical solution contains 43.5 mg of tavaborole. Inactive ingredients include alcohol 74.81 % (v/v), edetate calcium disodium, and propylene glycol.

12 CLINICAL PHARMACOLOGY

12.1 Mechanism of Action

Tavaborole is an oxaborole antifungal [see Clinical Pharmacology (12.4)].

12.2 Pharmacodynamics

At therapeutic doses, tavaborole topical solution is not expected to prolong QTc to any clinically relevant extent.

12.3 Pharmacokinetics

Tavaborole undergoes extensive metabolism. Renal excretion is the major route of elimination of the metabolites.

In a clinical pharmacology trial of six healthy adult male volunteers who received a single topical application of 5% ^14C-tavaborole solution, tavaborole conjugates and metabolites were shown to be excreted primarily in the urine.

The pharmacokinetics (PK) of tavaborole was investigated in 24 adult subjects with distal subungual onychomycosis involving at least 4 toenails (including at least 1 great toenail) following a single dose and a 2-week daily topical application of 200 μL of a 5% solution of tavaborole to all ten toenails and 2 mm of skin surrounding each toenail. Steady state was achieved after 14 days of dosing. After a single dose, the mean (± standard deviation) peak concentration (Cmax) of tavaborole was 3.5 ± 2.3 ng/mL (n=21 with measurable concentrations, range 0.618-10.2 ng/mL, LLOQ=0.5 ng/mL), and the mean AUClast ± SD was 44.4 ± 25.5 ng*hr/mL (n=21). After 2 weeks of daily dosing, the mean Cmax ± SD was 5.2 ± 3.5 ng/mL (n=24, range 1.5-12.8 ng/mL), and the mean AUCτ ± SD was 75.8 ± 44.5 ng*hr/mL.

In another study PK of tavaborole was investigated in 22 subjects aged 12 years to less than 17 years with distal subungual onychomycosis involving at least 4 toenails (including at least 1 great toenail with at least 20% involvement) following once daily application of 5% solution of tavaborole to all ten toenails and 2 mm of skin surrounding each toenail for 29 days. On Day 29, the mean ± SD Cmax was 5.9 ± 4.9 ng/mL (n=21 with measurable concentrations, range 1.0 -16.4 ng/mL, LLOQ=0.5 ng/mL), and the mean ± SD AUC0-24 was 76.0 ± 62.5 ng*hr/mL.

Drug Interaction Studies

In Vitro Studies

In vitro studies have shown that tavaborole, at therapeutic concentrations, neither inhibits nor induces cytochrome P450 (CYP450) enzymes.

12.4 Microbiology

Mechanism of Action

The mechanism of action of tavaborole is inhibition of fungal protein synthesis. Tavaborole inhibits protein synthesis by inhibition of an aminoacyl-transfer ribonucleic acid (tRNA) synthetase (AARS).

Activity in vitro and in clinical infections

Tavaborole has been shown to be active against most strains of the following microorganisms, both in vitro and in clinical infections [see Indications and Usage (1)]:

Trichophyton rubrum

Trichophyton mentagrophytes

Mechanism of Resistance

Trichophyton mentagrophytes and Trichophyton rubrum strains from isolates collected in the clinical trials have not demonstrated resistance following repeated exposure to tavaborole.

13 NONCLINICAL TOXICOLOGY

13.1 Carcinogenesis, Mutagenesis, Impairment of Fertility

In an oral carcinogenicity study in Sprague-Dawley rats, oral doses of 12.5, 25, and 50 mg/kg/day tavaborole were administered to rats once daily for 104 weeks. No drug related neoplastic findings were noted at oral doses up to 50 mg/kg/day tavaborole (14 times the MRHD based on AUC comparisons).

In a dermal carcinogenicity study in CD-1 mice, topical doses of 5%, 10%, and 15% tavaborole solution were administered to mice once daily for 104 weeks. No drug related neoplastic findings were noted at topical doses up to 15% tavaborole solution (89 times the MRHD based on AUC comparisons).

Tavaborole revealed no evidence of mutagenic or clastogenic potential based on the results of two in vitro genotoxicity tests (Ames assay and Human lymphocyte chromosomal aberration assay) and one in vivo genotoxicity test (rat micronucleus assay).

No effects on fertility were observed in male and female rats that were administered oral doses up to 300 mg/kg/day tavaborole (107 times the MRHD based on AUC comparisons) prior to and during early pregnancy.

14 CLINICAL STUDIES

The efficacy and safety of tavaborole topical solution was evaluated in two multicenter, double-blind, randomized, vehicle-controlled trials. Tavaborole topical solution or vehicle was applied once daily for 48 weeks in subjects with 20% to 60% clinical involvement of the target toenail, without dermatophytomas or lunula (matrix) involvement.

A total of 1194 subjects (795 tavaborole topical solution, 399 Vehicle) 18 to 88 years of age, 82% male, 84% white, participated in these two trials. Efficacy assessments were made at 52 weeks following a 48-week treatment period.

The Complete Cure efficacy endpoint included negative mycology (negative KOH wet mount and negative fungal culture) and Completely Clear Nail (no clinical evidence of onychomycosis as evidenced by a normal toenail plate, no onycholysis, and no subungual hyperkeratosis). Efficacy results from the two trials are summarized in Table 2.

Table 2: Efficacy Outcomes
Efficacy Variable | Trial 1 |  | Trial 2
Efficacy Variable | Tavaborole Topical Solution N=399 n (%) | Vehicle N=194 n (%) | Tavaborole Topical Solution N=396 n (%) | Vehicle N=205 n (%)
Complete Curea | 26 (6.5%) | 1 (0.5%) | 36 (9.1%) | 3 (1.5%)
Complete or Almost Complete Cureb | 61 (15.3%) | 3 (1.5%) | 71 (17.9%) | 8 (3.9%)
Mycologic Curec | 124 (31.1%) | 14 (7.2%) | 142 (35.9%) | 25 (12.2%)
a. Complete cure defined as 0% clinical involvement of the target toenail plus negative KOH and negative culture.
b. Complete or almost complete cure defined as ≤10% affected target toenail area involved and negative KOH and culture.
c. Mycologic cure defined as negative KOH and negative culture.

16 HOW SUPPLIED/STORAGE AND HANDLING

16.1 How Supplied

Tavaborole topical solution, 5% is a clear colorless alcohol-based solution supplied in an amber colored glass bottle with a black screw cap. At initial use, the screw cap is replaced with the dropper assembly. Rubber dropper with glass pipette packed in BOPP pouch printed with "THIS DEVICE CONTAINS DRY NATURAL RUBBER".

Tavaborole topical solution, 5% is supplied in the following presentations:

NDC 69097-686-37: One bottle containing 10 mL of solution with one glass pointed-tip dropper.

NDC 69097-686-34: One bottle containing 4 mL of solution with one glass pointed-tip dropper.

16.2 Storage and Handling

Store at 20°C–25°C (68°F–77°F); excursions permitted to 15°C–30°C (59°F–86°F) [see USP Controlled Room Temperature].

CAUTION: Flammable. Keep away from heat and flame.

Discard product within 3 months after insertion of the dropper.

Keep bottle tightly closed. Keep out of reach of children.

17 PATIENT COUNSELING INFORMATION

See FDA-approved patient labeling (Patient Information and Instructions for Use)

The patient should be told the following:

- The impact of nail polish or other cosmetic nail products on the efficacy of tavaborole has not been evaluated.
- Inform a health care professional if the area of application shows signs of persistent irritation (for example, redness, itching, swelling).
- Product is flammable. Avoid use near heat or open flame.

Manufactured by:

Encube Ethicals Pvt. Ltd,

Ponda, Goa-403 404, India

Manufactured for:

Cipla USA, Inc.

10 Independence Boulevard, Suite 300

Warren, NJ 07059

Revised: 01/2021

PATIENT INFORMATION
Tavaborole (TA va BOR ole) Topical Solution

Important information: Tavaborole topical solution is for use on toenails only. Do not use tavaborole topical solution in your mouth, eyes, or vagina.

What is tavaborole topical solution?
Tavaborole topical solution is a prescription medicine used to treat fungal infections of the toenails.
It is not known if tavaborole topical solution is safe and effective in children less than 6 years age.

Before using tavaborole topical solution, tell your healthcare provider about all of your medical conditions, including if you:
&#9679; are pregnant or plan to become pregnant. It is not known if tavaborole topical solution can harm your unborn baby.
&#9679; are breastfeeding or plan to breastfeed. It is not known if tavaborole passes into your breast milk. Talk to your healthcare provider about the best way to feed your baby during your treatment with tavaborole topical solution.
Tell your healthcare provider about all the medicines you take, including prescription and over-the-counter medicines, vitamins, and herbal supplements.

How should I use tavaborole topical solution?
See the "Instructions for Use" at the end of this Patient Information for detailed information about the right way to use tavaborole topical solution.
&#9679; Use tavaborole topical solution exactly as your healthcare provider tells you to use it.
&#9679; Apply tavaborole topical solution to your affected toenails 1 time each day.
&#9679; Tavaborole topical solution is used for 48 weeks.
&#9679; It is not known if the use of nail polish or other cosmetic nail products (such as gel nails or acrylic nails) will affect how tavaborole topical solution works.

What should I avoid while using tavaborole topical solution?
&#9679; Tavaborole topical solution is flammable. Avoid heat and flame while applying tavaborole topical solution to your toenail.

What are the possible side effects of tavaborole topical solution?
The most common side effects of tavaborole topical solution include: skin peeling, ingrown toenail, redness, itching, and swelling.
Tavaborole topical solution may cause irritation at or near the application site. Tell your healthcare provider if you develop irritation at the application site that does not go away. These are not all of the possible side effects of tavaborole topical solution.
Call your doctor for medical advice about side effects. You may report side effects to FDA at 1-800-FDA-1088.

How should I store tavaborole topical solution?
&#9679; Store tavaborole topical solution at room temperature, between 68°F to 77°F (20°C to 25°C).
&#9679; Tavaborole topical solution is flammable. Keep away from heat and flame.
&#9679; Keep the bottle tightly closed.
&#9679; Safely throw away tavaborole topical solution after 3 months of inserting the dropper.
Keep tavaborole topical solution and all medicines out of the reach of children.

General information about the safe and effective use of tavaborole topical solution
Medicines are sometimes prescribed for purposes other than those listed in a Patient Information leaflet. Do not use tavaborole topical solution for a condition for which it was not prescribed. Do not give tavaborole topical solution to other people, even if they have the same symptoms that you have. It may harm them. You can ask your pharmacist or healthcare provider for information about tavaborole topical solution that is written for health professionals.

What are the ingredients in tavaborole topical solution?
Active ingredient: tavaborole
Inactive ingredients: alcohol 74.81 % (v/v), edetate calcium disodium and propylene glycol
Manufactured by:
Encube Ethicals Pvt. Ltd,
Ponda, Goa-403 404, India
Manufactured for:
Cipla USA, Inc.
10 Independence Boulevard, Suite 300
Warren, NJ 07059
For more information, call 1-866-604-3268.

This Patient Information has been approved by the U.S. Food and Drug Administration.

Revised: 01/2021

Instructions for Use

Tavaborole (TA va BOR ole) Topical Solution

Important information: Tavaborole topical solution is for use on toenails only. Do not use tavaborole topical solution in your mouth, eyes, or vagina.

Read the Instructions for Use that comes with tavaborole topical solution before you start using it. Talk to your healthcare provider if you have any questions.

How to apply tavaborole topical solution:

Your toenails should be clean and dry before you apply tavaborole topical solution.

Step 1: | Before you apply tavaborole topical solution to your affected toenail for the first time, remove the cap from the tavaborole topical solution bottle. (See Figure A) Throw away the cap.
Step 2: | Remove the wrapping from the dropper that comes with tavaborole topical solution. Insert the dropper into the tavaborole topical solution bottle. (See Figure B)
 | Figure A Figure B
 | Only apply tavaborole topical solution using the provided dropper. Do not use the dropper for any other purpose.
Step 3: | With the dropper inserted into the tavaborole topical solution, squeeze the bulb and then release the bulb to draw tavaborole topical solution into the dropper.
Step 4: | Remove the dropper from the bottle and hold the dropper tip over your affected toenail.
Step 5: | Slowly squeeze the bulb to apply tavaborole topical solution to your toenail. Apply enough solution to completely cover your toenail. You may need to use more than one drop. (See Figure C)
 | Figure C
Step 6: | Use the dropper tip to gently spread tavaborole topical solution to cover the entire toenail up to the edges of the toenail. (See Figure D)
 | Figure D
Step 7: | In addition to the top of the toenail, also apply tavaborole topical solution under the tip of the toenail. Use the dropper tip to gently spread tavaborole topical solution under the entire tip of the toenail. (See Figures E and F)
 | Figure E Figure F
Step 8: | Repeat Steps 3 to 7 to apply tavaborole topical solution to each affected toenail.
Step 9: | Let the tavaborole topical solution dry completely. This may take a couple of minutes. Avoid getting tavaborole topical solution on skin that is not surrounding the treated toenail(s). If tavaborole topical solution comes in contact with surrounding skin, use a tissue to wipe any excess solution from the surrounding skin. Do not wipe tavaborole topical solution off of your toenails.
Step 10: | After applying tavaborole topical solution to your toenails, insert the dropper back into the bottle and screw it on tightly.
Step 11: | Wash your hands with soap and water after applying tavaborole topical solution. .

This Patient Information and Instructions for Use has been approved by the U.S. Food and Drug Administration.

Manufactured by:

Encube Ethicals Pvt. Ltd,

Ponda, Goa-403 404, India

Manufactured for:

Cipla USA, Inc.

10 Independence Boulevard, Suite 300

Warren, NJ 07059

Revised: 01/2021

PACKAGE LABEL.PRINCIPAL DISPLAY PANEL

NDC 69097-686-34

Rx Only

Tavaborole

Topical Solution

5 %

For Topical Use Only

Not for oral, ophthalmic,

or intravaginal use

4 mL

NDC 69097-686-34

Rx Only

Tavaborole

Topical Solution

5 %

For Topical Use Only

Not for oral, ophthalmic,

or intravaginal use

THIS PRODUCT DEVICE

CONTAINS DRY NATURAL RUBBER

4 mL

NDC 69097-686-37

Rx Only

Tavaborole

Topical Solution

5 %

For Topical Use Only

Not for oral, ophthalmic,

or intravaginal use

10 mL

NDC 69097-686-37

Rx Only

Tavaborole

Topical Solution

5 %

For Topical Use Only

Not for oral, ophthalmic,

or intravaginal use

THIS PRODUCT DEVICE

CONTAINS DRY NATURAL RUBBER

10 mL